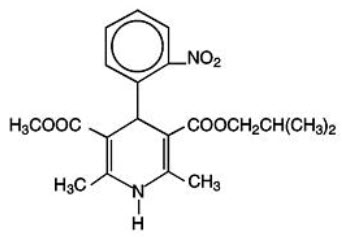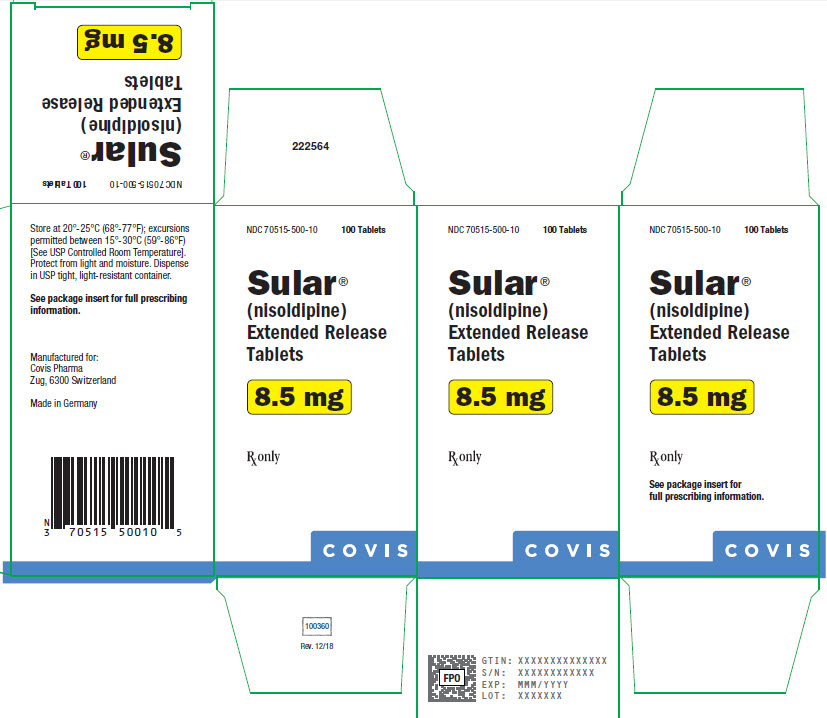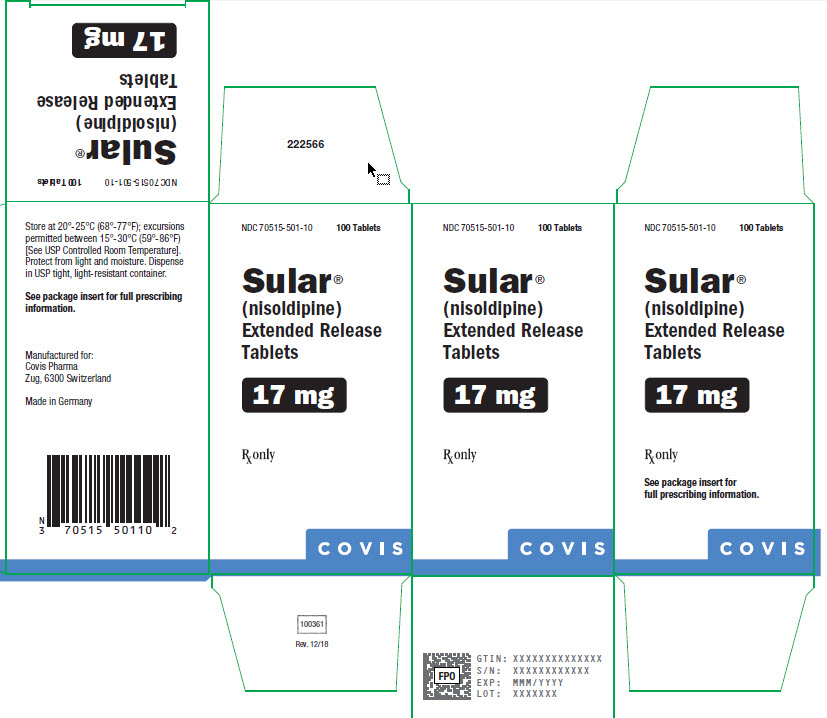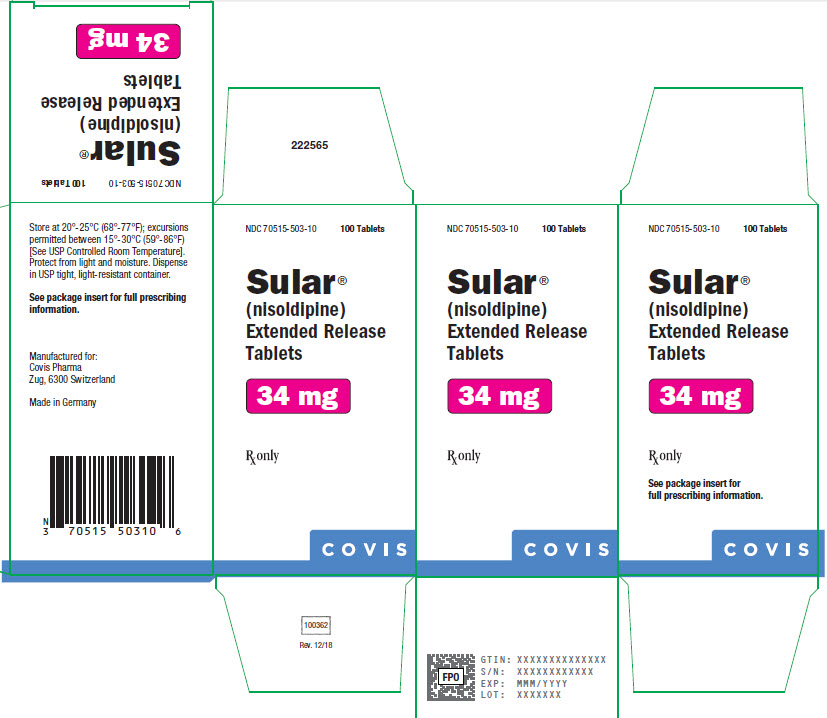 DRUG LABEL: Sular
NDC: 70515-500 | Form: TABLET, FILM COATED, EXTENDED RELEASE
Manufacturer: Covis Pharma US, Inc
Category: prescription | Type: HUMAN PRESCRIPTION DRUG LABEL
Date: 20230124

ACTIVE INGREDIENTS: NISOLDIPINE 8.5 mg/1 1
INACTIVE INGREDIENTS: HYPROMELLOSE, UNSPECIFIED; HYPROMELLOSE PHTHALATE (24% PHTHALATE, 55 CST); LACTOSE, UNSPECIFIED FORM; GLYCERYL DIBEHENATE; POVIDONE, UNSPECIFIED; MAGNESIUM STEARATE; SILICON DIOXIDE; METHACRYLIC ACID - METHYL METHACRYLATE COPOLYMER (1:2); SODIUM LAURYL SULFATE; POLYDEXTROSE; TITANIUM DIOXIDE; POLYETHYLENE GLYCOL, UNSPECIFIED; FERRIC OXIDE RED; CARNAUBA WAX

SULAR® (nisoldipine)
Extended Release Tablets
For Oral Use

DESCRIPTION

SULAR® (nisoldipine) is an extended release tablet dosage form of the dihydropyridine calcium channel blocker nisoldipine. Nisoldipine is 3,5-pyridinedicarboxylic acid, 1,4-dihydro-2,6-dimethyl-4-(2-nitrophenyl)-, methyl 2-methylpropyl ester, C20H24N2O6, and has the structural formula:

Nisoldipine is a yellow crystalline substance, practically insoluble in water but soluble in ethanol. It has a molecular weight of 388.4. SULAR tablets comprise three layers: a top barrier layer, a middle layer containing nisoldipine, and a bottom barrier layer. The erodible barrier layers and the hydrogel middle layer provide for the controlled release of the drug. SULAR tablets contain either 8.5, 17, or 34 mg of nisoldipine for once-a-day oral administration.

Inactive ingredients in the formulation include: Hypromellose, hypromellose phthalate, lactose, glyceryl behenate, povidone, magnesium stearate, silicon dioxide, methacrylic acid copolymer, and sodium lauryl sulfate. Inactive ingredients in the film coating include: polydextrose, titanium dioxide, hypromellose, polyethylene glycol, iron oxide, and carnauba wax. Additionally, the 17 mg formulation contains FD&C Yellow #5.

CLINICAL PHARMACOLOGY

Mechanism of Action

Nisoldipine is a member of the dihydropyridine class of calcium channel antagonists (calcium ion antagonists or slow channel blockers) that inhibit the transmembrane influx of calcium into vascular smooth muscle and cardiac muscle. It reversibly competes with other dihydropyridines for binding to the calcium channel. Because the contractile process of vascular smooth muscle is dependent upon the movement of extracellular calcium into the muscle through specific ion channels, inhibition of the calcium channel results in dilation of the arterioles. In vitro studies show that the effects of nisoldipine on contractile processes are selective, with greater potency on vascular smooth muscle than on cardiac muscle. Although, like other dihydropyridine calcium channel blockers, nisoldipine has negative inotropic effects in vitro, studies conducted in intact anesthetized animals have shown that the vasodilating effect occurs at doses lower than those that affect cardiac contractility.

The effect of nisoldipine on blood pressure is principally a consequence of a dose-related decrease of peripheral vascular resistance. While nisoldipine, like other dihydropyridines, exhibits a mild diuretic effect, most of the antihypertensive activity is attributed to its effect on peripheral vascular resistance.

Pharmacokinetics and Metabolism

Nisoldipine pharmacokinetics are independent of the dose across the clinical dosage range of 17 to 51 mg, with plasma concentrations proportional to dose. Nisoldipine accumulation, during multiple dosing, is predictable from a single dose. Nisoldipine is relatively well absorbed into the systemic circulation with 87% of the radiolabeled drug recovered in urine and feces. The absolute bioavailability of nisoldipine is about 5%. Nisoldipine's low bioavailability is due, in part, to pre-systemic metabolism in the gut wall, and this metabolism decreases from the proximal to the distal parts of the intestine. A pronounced food-effect is observed when SULAR is administered with a high-fat meal resulting in an increased peak concentration (Cmax) of up to 245%. Total exposure (AUC) is decreased by 25%. As a result, SULAR should be taken on an empty stomach (1 hour before or 2 hours after a meal).

Maximal plasma concentrations of nisoldipine are reached at 9.2 ± 5.1 hours. The terminal elimination half-life (reflecting post absorption clearance of nisoldipine) ranges from 13.7 ± 4.3 hours. After oral administration, the concentration of (+)-nisoldipine, the active enantiomer, is about 6 times higher than the inactive (-) -nisoldipine enantiomer. The plasma protein binding of nisoldipine is very high, with less than 1% unbound over the plasma concentration range of 100 ng/mL to 10 mcg/mL.

Nisoldipine is highly metabolized; 5 major urinary metabolites have been identified. Although 60 - 80% of an oral dose undergoes urinary excretion, only traces of unchanged nisoldipine are found in urine. The major biotransformation pathway appears to be the hydroxylation of the isobutyl ester. A hydroxylated derivative of the side chain, present in plasma at concentrations approximately equal to the parent compound, appears to be the only active metabolite, and has about 10% of the activity of the parent compound. Cytochrome P450 enzymes are believed to play a major role in the metabolism of nisoldipine. The particular isoenzyme system responsible for its metabolism has not been identified, but other dihydropyridines are metabolized by cytochrome P450 IIIA4. Nisoldipine should not be administered with grapefruit juice, as this has been shown, in a study of 12 subjects, to interfere with nisoldipine metabolism, resulting in a mean increase in Cmax of about 3-fold (ranging up to about 7-fold) and AUC of almost 2-fold (ranging up to about 5-fold). A similar phenomenon has been seen with several other dihydropyridine calcium channel blockers.

Special Populations

Renal Dysfunction

Because renal elimination is not an important pathway, bioavailability and pharmacokinetics of SULAR were not significantly different in patients with various degrees of renal impairment. Dosing adjustments in patients with mild to moderate renal impairment are not necessary.

Geriatric

Elderly patients have been found to have 2 to 3 fold higher plasma concentrations (Cmax and AUC) than young subjects. This should be reflected in more cautious dosing (see DOSAGE AND ADMINISTRATION).

Hepatic Insufficiency

In patients with liver cirrhosis given a dose bioequivalent to 8.5 mg SULAR, plasma concentrations of the parent compound were 4 to 5 times higher than those in healthy young subjects. Lower starting and maintenance doses should be used in cirrhotic patients (see DOSAGE AND ADMINISTRATION).

Gender and Race

The effect of gender or race on the pharmacokinetics of nisoldipine has not been investigated.

Disease States

Hypertension does not significantly alter the pharmacokinetics of nisoldipine.

Pharmacodynamics

Hemodynamic Effects

Administration of a single dose of nisoldipine leads to decreased systemic vascular resistance and blood pressure with a transient increase in heart rate. The change in heart rate is greater with immediate release nisoldipine preparations. The effect on blood pressure is directly related to the initial degree of elevation above normal. Chronic administration of nisoldipine results in a sustained decrease in vascular resistance and small increases in stroke index and left ventricular ejection fraction. A study of the immediate release formulation showed no effect of nisoldipine on the renin-angiotensin-aldosterone system or on plasma norepinephrine concentration in normals. Changes in blood pressure in hypertensive patients given SULAR were dose related over the clinical dosage range.

Nisoldipine does not appear to have significant negative inotropic activity in intact animals or humans, and did not lead to worsening of clinical heart failure in three small studies of patients with asymptomatic and symptomatic left ventricular dysfunction. There is little information, however, in patients with severe congestive heart failure, and all calcium channel blockers should be used with caution in any patient with heart failure.

Electrophysiologic Effects

Nisoldipine has no clinically important chronotropic effects. Except for mild shortening of sinus cycle, SA conduction time and AH intervals, single oral doses up to 20 mg of immediate release nisoldipine did not significantly change other conduction parameters. Similar electrophysiologic effects were seen with single IV doses, which could be blunted in patients pre-treated with beta-blockers. Dose and plasma level related flattening or inversion of T-waves have been observed in a few small studies. Such reports were concentrated in patients receiving rapidly increased high doses in one study; the phenomenon has not been a cause of safety concern in large clinical trials.

Clinical Studies in Hypertension

The antihypertensive efficacy of SULAR was studied in 5 double-blind, placebo-controlled, randomized studies, in which over 600 patients were treated with SULAR as monotherapy and about 300 with placebo; 4 of the five studies compared 2 or 3 fixed doses while the fifth allowed titration from doses bioequivalent to 8.5 - 34 mg. Once daily administration of SULAR produced sustained reductions in systolic and diastolic blood pressures over the 24 hour dosing interval in both supine and standing positions. The mean placebo-subtracted reductions in supine systolic and diastolic blood pressure at trough, 24 hours post-dose, in these studies, are shown below. Changes in standing blood pressure were similar:

MEAN SUPINE TROUGH SYSTOLIC AND DIASTOLIC BLOOD PRESSURE CHANGES (mm Hg)
SULAR
Doses bioequivalent to: (mg/day) | 8.5 mg | 17 mg | 25.5 mg | 34 mg | 8.5-34 mg titrated
Systolic | 8 | 11 | 11 | 14 | 15
Diastolic | 3 | 5 | 7 | 7 | 8

In patients receiving atenolol, supine blood pressure reductions with SULAR at doses bioequivalent to 17 and 34 mg once daily were 12/6 and 19/8 mm Hg, respectively. The sustained antihypertensive effect of SULAR was demonstrated by 24 hour blood pressure monitoring and examination of peak and trough effects. The trough/peak ratios ranged from 70 to 100% for diastolic and systolic blood pressure. The mean change in heart rate in these studies was less than one beat per minute. In 4 of the 5 studies, patients received initial doses bioequivalent to 17-25.5 mg SULAR without incident (excessive effects on blood pressure or heart rate). The fifth study started patients on lower doses of SULAR.

Patient race and gender did not influence the blood pressure lowering effect of SULAR. Despite the higher plasma concentration of nisoldipine in the elderly, there was no consistent difference in their blood pressure response except that the lowest clinical dose was somewhat more effective than in non-elderly patients. No postural effect on blood pressure was apparent and there was no evidence of tolerance to the antihypertensive effect of SULAR in patients treated for up to one year.

INDICATIONS AND USAGE

SULAR is indicated for the treatment of hypertension. It may be used alone or in combination with other antihypertensive agents.

CONTRAINDICATIONS

SULAR is contraindicated in patients with known hypersensitivity to dihydropyridine calcium channel blockers.

WARNINGS

Increased angina and/or myocardial infarction in patients with coronary artery disease:

Rarely, patients, particularly those with severe obstructive coronary artery disease, have developed increased frequency, duration and/or severity of angina, or acute myocardial infarction on starting calcium channel blocker therapy or at the time of dosage increase. The mechanism of this effect has not been established. In controlled studies of SULAR in patients with angina this was seen about 1.5% of the time in patients given nisoldipine, compared with 0.9% in patients given placebo.

PRECAUTIONS

General

Hypotension

Because nisoldipine, like other vasodilators, decreases peripheral vascular resistance, careful monitoring of blood pressure during the initial administration and titration of SULAR is recommended. Close observation is especially important for patients already taking medications that are known to lower blood pressure. Although in most patients the hypotensive effect of SULAR is modest and well tolerated, occasional patients have had excessive and poorly tolerated hypotension. These responses have usually occurred during initial titration or at the time of subsequent upward dosage adjustment.

Congestive Heart Failure

Although acute hemodynamic studies of nisoldipine in patients with NYHA Class II-IV heart failure have not demonstrated negative inotropic effects, safety of SULAR in patients with heart failure has not been established. Caution therefore should be exercised when using SULAR in patients with heart failure or compromised ventricular function, particularly in combination with a beta-blocker.

Patients with Hepatic Impairment

Because nisoldipine is extensively metabolized by the liver and, in patients with cirrhosis, it reaches blood concentrations about 5 times those in normals, SULAR should be administered cautiously in patients with severe hepatic dysfunction (see DOSAGE AND ADMINISTRATION).

Information for Patients

SULAR is an extended release tablet and should be swallowed whole. Tablets should not be chewed, divided or crushed. SULAR should be taken on an empty stomach (1 hour before or 2 hours after a meal). Grapefruit juice, which has been shown to increase significantly the bioavailability of nisoldipine and other dihydropyridine type calcium channel blockers, should not be taken with SULAR.

This product contains FD&C Yellow No. 5 (tartrazine) which may cause allergic-type reactions (including bronchial asthma) in certain susceptible persons. Although the overall incidence of FD&C Yellow No. 5 (tartrazine) sensitivity in the general population is low, it is frequently seen in patients who also have aspirin hypersensitivity.

Laboratory Tests

SULAR is not known to interfere with the interpretation of laboratory tests.

Drug Interactions

A 30 to 45% increase in AUC and Cmax of nisoldipine was observed with concomitant administration of cimetidine 400 mg twice daily. Ranitidine 150 mg twice daily did not interact significantly with nisoldipine (AUC was decreased by 15 - 20%). No pharmacodynamic effects of either histamine H2 receptor antagonist were observed.

CYP3A4 inhibitors and inducers

SULAR is substrate of CYP3A4 and coadministration of SULAR with any known inducer or inhibitor of CYP3A4 should be avoided in general.

Coadministration of phenytoin with a dose bioequivalent to 34 mg SULAR tablets in epileptic patients lowered the nisoldipine plasma concentrations to undetectable levels. Coadministration of SULAR with phenytoin should be avoided and alternative antihypertensive therapy should be considered. Pharmacokinetic interactions between nisoldipine and beta-blockers (atenolol, propranolol) were variable and not significant. Propranolol attenuated the heart rate increase following administration of immediate release nisoldipine. The blood pressure effect of SULAR tended to be greater in patients on atenolol than in patients on no other antihypertensive therapy. Quinidine at 648 mg bid decreased the bioavailability (AUC) of nisoldipine by 26%, but not the peak concentration. Immediate release nisoldipine increased plasma quinidine concentrations by about 20%. This interaction was not accompanied by ECG changes and its clinical significance is not known. No significant interactions were found between nisoldipine and warfarin or digoxin.

Carcinogenesis, Mutagenesis, Impairment of Fertility

Dietary administration of nisoldipine to male and female rats for up to 24 months (mean doses up to 82 and 111 mg/kg/day, 16 and 19 times the maximum recommended human dose [MRHD] on a mg/m^2 basis, respectively) and female mice for up to 21 months (mean doses of up to 217 mg/kg/day, 20 times the MRHD on a mg/m^2 basis) revealed no evidence of tumorigenic effect of nisoldipine. In male mice receiving a mean dose of 163 mg nisoldipine/kg/day (16 times the MRHD of 60 mg/day on a mg/m^2 basis), an increased frequency of stomach papilloma, but still within the historical range, was observed. No evidence of stomach neoplasia was observed at lower doses (up to 58 mg/kg/day). Nisoldipine was negative when tested in a battery of genotoxicity assays including the Ames test and the CHO/HGRPT assay for mutagenicity and the in vivo mouse micronucleus test and in vitro CHO cell test for clastogenicity.

When administered to male and female rats at doses of up to 30 mg/kg/day (about 5 times the MRHD on a mg/m^2 basis) nisoldipine had no effect on fertility.

Pregnancy

Nisoldipine was neither teratogenic nor fetotoxic at doses that were not maternally toxic. Nisoldipine was fetotoxic but not teratogenic in rats and rabbits at doses resulting in maternal toxicity (reduced maternal body weight gain). In pregnant rats, increased fetal resorption (postimplantation loss) was observed at 100 mg/kg/day and decreased fetal weight was observed at both 30 and 100 mg/kg/day. These doses are, respectively, about 5 and 16 times the MRHD when compared on a mg/m^2 basis. In pregnant rabbits, decreased fetal and placental weights were observed at a dose of 30 mg/kg/day, about 10 times the MRHD when compared on a mg/m^2 basis. In a study in which pregnant monkeys (both treated and control) had high rates of abortion and mortality, the only surviving fetus from a group exposed to a maternal dose of 100 mg nisoldipine/kg/day (about 30 times the MRHD when compared on a mg/m^2 basis) presented with forelimb and vertebral abnormalities not previously seen in control monkeys of the same strain. There are no adequate and well controlled studies in pregnant women. SULAR should be used in pregnancy only if the potential benefit justifies the potential risk to the fetus.

Nursing Mothers

It is not known whether nisoldipine is excreted in human milk. Because many drugs are excreted in human milk, a decision should be made to discontinue nursing, or to discontinue SULAR, taking into account the importance of the drug to the mother.

Pediatric Use

Safety and effectiveness in pediatric patients have not been established.

Geriatric Use

Clinical studies of nisoldipine did not include sufficient numbers of subjects aged 65 and over to determine whether they respond differently from younger subjects. Other reported clinical experience has not identified differences in responses between the elderly and younger patients. Patients over 65 are expected to develop higher plasma concentrations of nisoldipine. In general, dose selection for an elderly patient should be cautious, usually starting at the low end of the dosing range, reflecting the greater frequency of decreased hepatic, renal or cardiac function, and of concomitant disease or other drug therapy.

ADVERSE EXPERIENCES

More than 6000 patients world-wide have received nisoldipine in clinical trials for the treatment of hypertension, either as the immediate release or the SULAR extended release formulation. Of about 1,500 patients who received SULAR in hypertension studies, about 55% were exposed for at least 2 months and about one third were exposed for over 6 months, the great majority at doses equivalent to 17 mg and above.

SULAR is generally well-tolerated. In the U.S. clinical trials of SULAR in hypertension, 10.9% of the 921 SULAR patients discontinued treatment due to adverse events compared with 2.9% of 280 placebo patients. The frequency of discontinuations due to adverse experiences was related to dose, with a 5.4% and 10.9% discontinuation rate at the lowest and highest daily dose, respectively.

The most frequently occurring adverse experiences with SULAR are those related to its vasodilator properties; these are generally mild and only occasionally lead to patient withdrawal from treatment. The table below, from U.S. placebo-controlled parallel dose response trials of SULAR using doses across the clinical dosage range in patients with hypertension, lists all of the adverse events, regardless of the causal relationship to SULAR, for which the overall incidence on SULAR was both >1% and greater with SULAR than with placebo.

Adverse Event | Nisoldipine (%) (n=663) | Placebo (%) (n=280)
Peripheral Edema | 22 | 10
Headache | 22 | 15
Dizziness | 5 | 4
Pharyngitis | 5 | 4
Vasodilation | 4 | 2
Sinusitis | 3 | 2
Palpitation | 3 | 1
Chest Pain | 2 | 1
Nausea | 2 | 1
Rash | 2 | 1
Only peripheral edema and possibly dizziness appear to be dose related.

Adverse Event | SULAR, dose bioequivalent to:
Adverse Event | Placebo | 8.5mg | 17mg | 25.5mg | 34mg
(Rates in %) | N=280 | N=30 | N=170 | N=105 | N=139
Peripheral Edema | 10 | 7 | 15 | 20 | 27
Dizziness | 4 | 7 | 3 | 3 | 4

The common adverse events occurred at about the same rate in men as in women, and at a similar rate in patients over age 65 as in those under that age, except that headache was much less common in older patients. Except for peripheral edema and vasodilation, which were more common in whites, adverse event rates were similar in blacks and whites.

The following adverse events occurred in ≤1% of all patients treated for hypertension in U.S. and foreign clinical trials, or with unspecified incidence in other studies. Although a causal relationship of SULAR to these events cannot be established, they are listed to alert the physician to a possible relationship with SULAR treatment.

Body As A Whole: cellulitis, chills, facial edema, fever, flu syndrome, malaise

Cardiovascular: atrial fibrillation, cerebrovascular accident, congestive heart failure, first degree AV block, hypertension, hypotension, jugular venous distension, migraine, myocardial infarction, postural hypotension, ventricular extrasystoles, supraventricular tachycardia, syncope, systolic ejection murmur, T wave abnormalities on ECG (flattening, inversion, nonspecific changes), venous insufficiency

Digestive: abnormal liver function tests, anorexia, colitis, diarrhea, dry mouth, dyspepsia, dysphagia, flatulence, gastritis, gastrointestinal hemorrhage, gingival hyperplasia, glossitis, hepatomegaly, increased appetite, melena, mouth ulceration

Endocrine: diabetes mellitus, thyroiditis

Hemic and Lymphatic: anemia, ecchymoses, leukopenia, petechiae

Metabolic and Nutritional: gout, hypokalemia, increased serum creatine kinase, increased nonprotein nitrogen, weight gain, weight loss

Musculoskeletal: arthralgia, arthritis, leg cramps, myalgia, myasthenia, myositis, tenosynovitis

Nervous: abnormal dreams, abnormal thinking and confusion, amnesia, anxiety, ataxia, cerebral ischemia, decreased libido, depression, hypesthesia, hypertonia, insomnia, nervousness, paresthesia, somnolence, tremor, vertigo

Respiratory: asthma, dyspnea, end inspiratory wheeze and fine rales, epistaxis, increased cough, laryngitis, pharyngitis, pleural effusion, rhinitis, sinusitis

Skin and Appendages: acne, alopecia, dry skin, exfoliative dermatitis, fungal dermatitis, herpes simplex, herpes zoster, maculopapular rash, pruritus, pustular rash, skin discoloration, skin ulcer, sweating, urticaria

Special Senses: abnormal vision, amblyopia, blepharitis, conjunctivitis, ear pain, glaucoma, itchy eyes, keratoconjunctivitis, otitis media, retinal detachment, tinnitus, watery eyes, taste disturbance, temporary unilateral loss of vision, vitreous floater

Urogenital: dysuria, hematuria, impotence, nocturia, urinary frequency, increased BUN and serum creatinine, vaginal hemorrhage, vaginitis

The following postmarketing event has been reported very rarely in patients receiving SULAR: systemic hypersensitivity reaction which may include one or more of the following; angioedema, shortness of breath, tachycardia, chest tightness, hypotension, and rash. A definite causal relationship with SULAR has not been established. An unusual event observed with immediate release nisoldipine but not observed with SULAR was one case of photosensitivity. Gynecomastia has been associated with the use of calcium channel blockers.

OVERDOSAGE

There is no experience with nisoldipine overdosage. Generally, overdosage with other dihydropyridines leading to pronounced hypotension calls for active cardiovascular support including monitoring of cardiovascular and respiratory function, elevation of extremities, judicious use of calcium infusion, pressor agents and fluids. Clearance of nisoldipine would be expected to be slowed in patients with impaired liver function. Since nisoldipine is highly protein bound, dialysis is not likely to be of any benefit; however, plasmapheresis may be beneficial.

DOSAGE AND ADMINISTRATION

The dosage of SULAR must be adjusted to each patient's needs. Therapy usually should be initiated with 17 mg orally once daily, then increased by 8.5 mg per week or longer intervals, to attain adequate control of blood pressure. Usual maintenance dosage is 17 to 34 mg once daily. Blood pressure response increases over the 8.5 - 34 mg daily dose range but adverse event rates also increase. Doses beyond 34 mg once daily are not recommended. SULAR has been used safely with diuretics, ACE inhibitors, and beta-blocking agents. Patients over age 65, or patients with impaired liver function, are expected to develop higher plasma concentrations of nisoldipine. Their blood pressure should be monitored closely during any dosage adjustment. A starting dose not exceeding 8.5 mg daily is recommended in these patient groups. SULAR tablets should be administered orally once daily. SULAR should be taken on an empty stomach (1 hour before or 2 hours after a meal). Grapefruit products should be avoided before and after dosing. SULAR is an extended release dosage form and tablets should be swallowed whole, not bitten, divided or crushed.

HOW SUPPLIED

SULAR extended release tablets are supplied as 8.5 mg and 17 mg round film coated tablets and 34 mg elliptic film coated tablets. The different strengths can be identified as follows:

Strength | Color | Markings
8.5 mg | Oyster | SCI 500
17 mg | Yellow Cream | SCI 501
34 mg | Burnt Orange | SCI 503

SULAR Tablets are supplied in bottles of 100:

NDC Code | Strength
70515-500-10 | 8.5 mg
70515-501-10 | 17 mg
70515-503-10 | 34 mg

Protect from light and moisture. Store at 20°-25°C (68°-77°F); excursions permitted to 15°-30°C (59°-86°F) [see USP Controlled Room Temperature]. Dispense in tight, light-resistant containers.

Rx only

Sular is a trademark of Covis Pharma
©2017 Covis Pharma.

Manufactured for:
Covis Pharma
Zug, 6300 Switzerland

Made in Germany

Rev 07/17

PRINCIPAL DISPLAY PANEL - 8.5 mg Carton

8.5 mg Carton

NDC 70515-500-10

100 Tablets

Sular®
(nisoldipine)
Extended Release
Tablets

8.5 mg

Rx only

See package insert for full prescribing
information.

COVIS

Store at 20°-25°C (68°-77°F); excursions
permitted between 15°-30°C (59°-86°F)
[See USP Controlled Room Temperature].
Protect from light and moisture. Dispense
in USP tight, light-resistant container.

See package insert for full prescribing
information.

Manufactured for:
Covis Pharma
Zug, 6300 Switzerland

Made in Germany

GTIN: XXXXXXXXXXXXXX
S/N: XXXXXXXXXXXX
EXP: MMM/YYYY
LOT: XXXXXXX

PRINCIPAL DISPLAY PANEL - 17 mg Carton

17 mg Carton

NDC 70515-501-10

100 Tablets

Sular®
(nisoldipine)
Extended Release
Tablets

17 mg

Rx only

See package insert for full prescribing
information.

COVIS

Store at 20°-25°C (68°-77°F); excursions
permitted between 15°-30°C (59°-86°F)
[See USP Controlled Room Temperature].
Protect from light and moisture. Dispense
in USP tight, light-resistant container.

See package insert for full prescribing
information.

Manufactured for:
Covis Pharma
Zug, 6300 Switzerland

Made in Germany

GTIN: XXXXXXXXXXXXXX
S/N: XXXXXXXXXXXX
EXP: MMM/YYYY
LOT: XXXXXXX

PRINCIPAL DISPLAY PANEL - 34 mg Carton

34 mg Carton

NDC 70515-503-10

100 Tablets

Sular®
(nisoldipine)
Extended Release
Tablets

34 mg

Rx only

See package insert for full prescribing
information.

COVIS

Store at 20°-25°C (68°-77°F); excursions
permitted between 15°-30°C (59°-86°F)
[See USP Controlled Room Temperature].
Protect from light and moisture. Dispense
in USP tight, light-resistant container.

See package insert for full prescribing
information.

Manufactured for:
Covis Pharma
Zug, 6300 Switzerland

Made in Germany

GTIN: XXXXXXXXXXXXXX
S/N: XXXXXXXXXXXX
EXP: MMM/YYYY
LOT: XXXXXXX